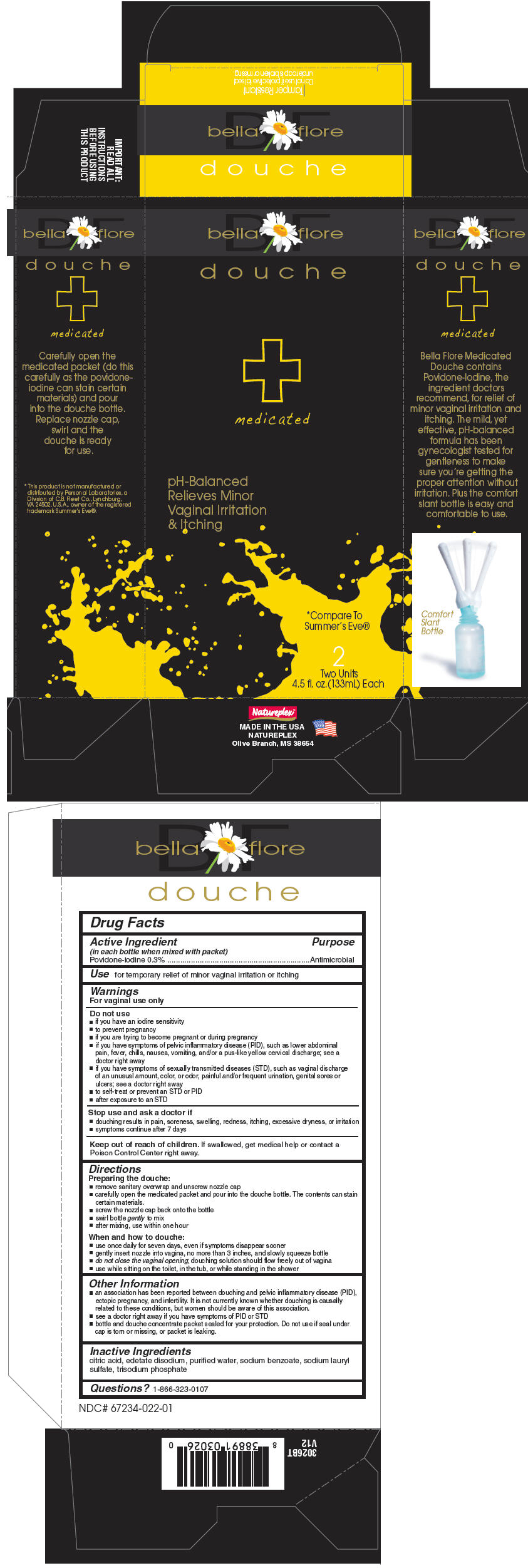 DRUG LABEL: Bella Flore
NDC: 67234-022 | Form: KIT | Route: VAGINAL
Manufacturer: Natureplex LLC
Category: otc | Type: HUMAN OTC DRUG LABEL
Date: 20210201

ACTIVE INGREDIENTS: POVIDONE-IODINE 0.3 g/100 mL
INACTIVE INGREDIENTS: EDETATE DISODIUM; COCO DIETHANOLAMIDE; SODIUM BENZOATE; SODIUM LAURETH-3 SULFATE; SODIUM PHOSPHATE, TRIBASIC; CITRIC ACID MONOHYDRATE; WATER; COCAMIDOPROPYL BETAINE

Bella Flore
Medicated Douche

Drug Facts

Active ingredient (in each bottle when mixed with packet)

Povidone-iodine 0.3%

Purpose

Antimicrobial

Use

for temporary relief of minor vaginal irritation or itching

Warnings

For vaginal use only

Do not use

- if you have an iodine sensitivity
- to prevent pregnancy
- if you are trying to become pregnant or during pregnancy
- if you have symptoms of pelvic inflammatory disease (PID), such as lower abdominal pain, fever, chills, nausea, vomiting, and/or a pus-like yellow cervical discharge; see a doctor right away
- if you have symptoms of sexually transmitted
- diseases (STD), such as vaginal discharge of an unusual amount, color, or odor, painful and/or frequent urination, genital sores or ulcers; see a doctor right away to self-treat or prevent an STD or PID after exposure to an STD

Stop use and ask a doctor if

- douching results in pain, soreness, swelling, redness, itching, excessive dryness, or irritation
- symptoms continue after 7 days

Keep out of reach of children. If swallowed, get medical help or contact a Poison Control Center right away.

Directions

Preparing the douche

- remove sanitary overwrap and unscrew nozzle cap
- carefully open the medicated packet and pour into the douche bottle. The contents can stain certain materials.
- screw the nozzle cap back onto the bottle
- swirl bottle gently to mix
- after mixing, use within one hour

When and how to douche

- use once daily for seven days, even if symptoms disappear sooner
- gently insert nozzle into vagina, no more than 3 inches, and slowly squeeze bottle
- do not close the vaginal opening; douching solution should flow freely out of vagina
- use while sitting on the toilet, in the tub, or while standing in the shower

Other information

- an association has been reported between douching and pelvic inflammatory disease (PID), ectopic pregnancy, and infertility. It is not currently known whether douching is causally related to these conditions, but women should be aware of this association.
- see a doctor right away if you have symptoms of PID or STD
- bottle and douche concentrate packet sealed for your protection. Do not use if seal under cap is torn or missing, or packet is leaking.

Inactive ingredients

citric acid, edetate disodium, purified water, sodium benzoate, sodium lauryl sulfate, trisodium phosphate

Questions?

1-866-323-0107

PRINCIPAL DISPLAY PANEL - 133 mL Kit Carton

bella flore

douche

medicated

pH-Balanced
Relieves Minor
Vaginal Irritation
& Itching

*Compare To
Summer's Eve®

2
Two Unit
4.5 fl. oz.(133mL)